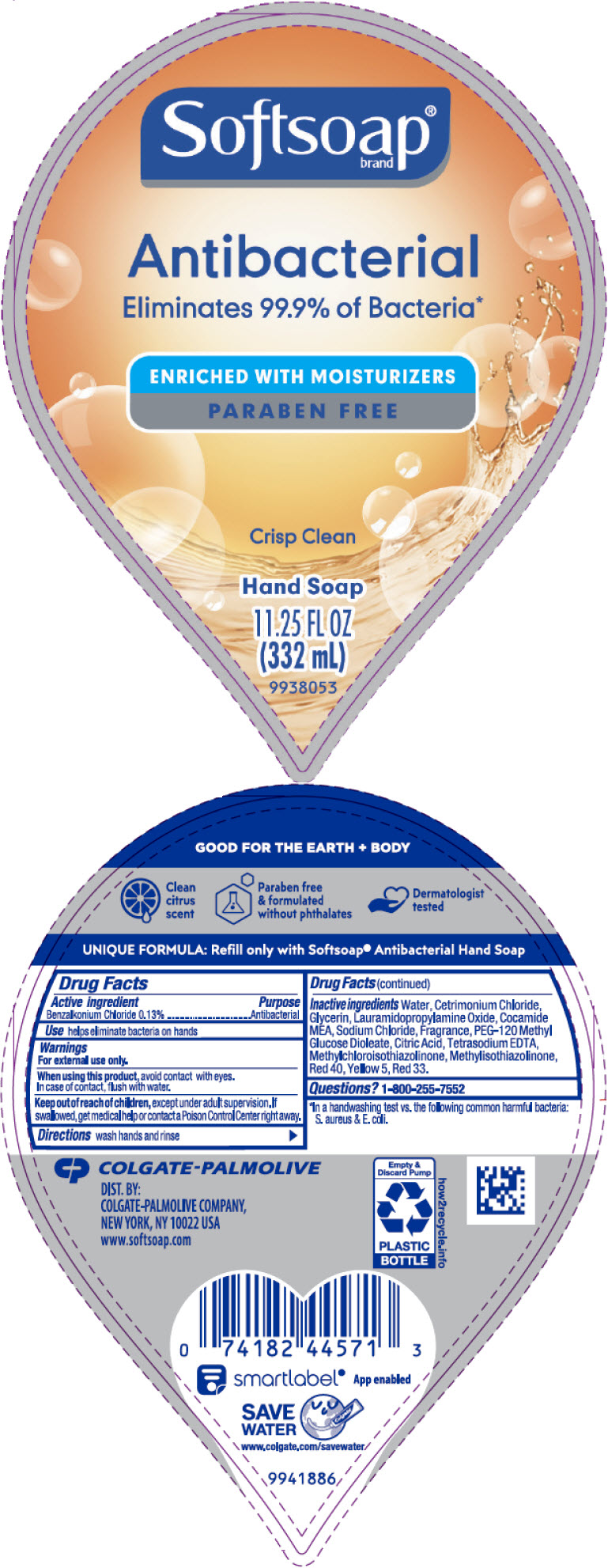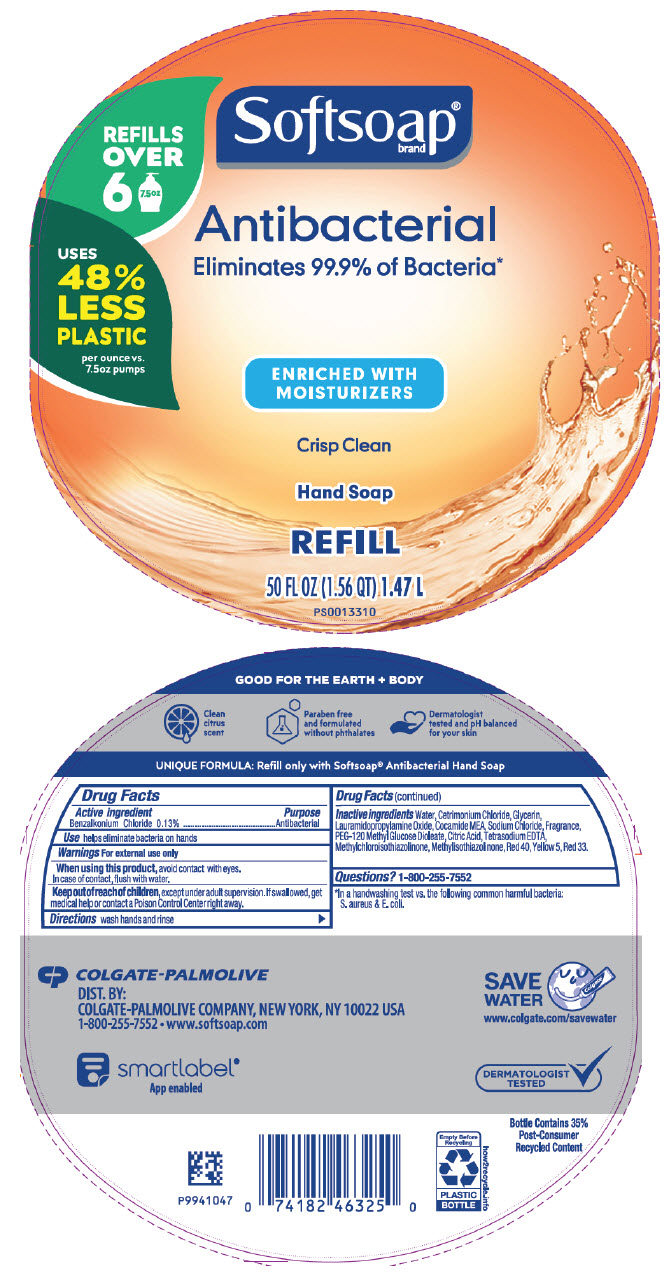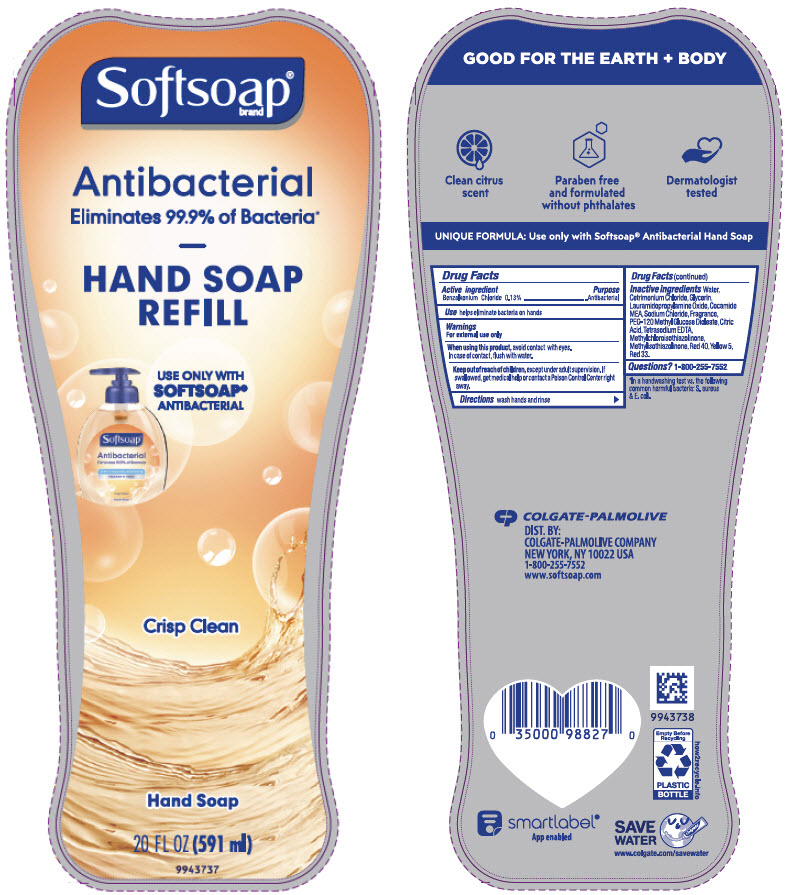 DRUG LABEL: Softsoap Antibacterial with Moisturizers Crisp Clean LHS
NDC: 35000-100 | Form: LIQUID
Manufacturer: COLGATE PALMOLIVE COMPANY
Category: otc | Type: HUMAN OTC DRUG LABEL
Date: 20200901

ACTIVE INGREDIENTS: BENZALKONIUM CHLORIDE 1.33 mg/1 mL
INACTIVE INGREDIENTS: WATER; CETRIMONIUM CHLORIDE; GLYCERIN; LAURAMIDOPROPYLAMINE OXIDE; COCO MONOETHANOLAMIDE; SODIUM CHLORIDE; PEG-120 METHYL GLUCOSE DIOLEATE; CITRIC ACID MONOHYDRATE; EDETATE SODIUM; METHYLCHLOROISOTHIAZOLINONE; METHYLISOTHIAZOLINONE; FD&C RED NO. 40; FD&C YELLOW NO. 5; D&C RED NO. 33

Softsoap® Antibacterial with Moisturizers Crisp Clean

Drug Facts

Active ingredient

Benzalkonium Chloride 0.13%

Purpose

Antibacterial

Use

helps eliminate bacteria on hands

Warnings

For external use only

When using this product, avoid contact with eyes.

In case of contact, flush with water.

Keep out of reach of children, except under adult supervision. If swallowed, get medical help or contact a Poison Control Center right away.

Directions

wash hands and rinse

Inactive ingredients

Water, Cetrimonium Chloride, Glycerin, Lauramidopropylamine Oxide, Cocamide MEA, Sodium Chloride, Fragrance, PEG-120 Methyl Glucose Dioleate, Citric Acid, Tetrasodium EDTA, Methylchloroisothiazolinone, Methylisothiazolinone, Red 40, Yellow 5, Red 33.

Questions?

1-800-255-7552

DIST. BY:
COLGATE-PALMOLIVE COMPANY,
NEW YORK, NY 10022 USA

PRINCIPAL DISPLAY PANEL - 332 mL Bottle Label

Softsoap®
brand

Antibacterial
Eliminates 99.9% of Bacteria*

ENRICHED WITH MOISTURIZERS
PARABEN FREE

Crisp Clean

Hand Soap
11.25 FL OZ
(332 mL)
9938053

PRINCIPAL DISPLAY PANEL - 1.47 L Bottle Label

REFILLS
OVER
6
7.5oz

Softsoap®
brand

Antibacterial
Eliminates 99.9% of Bacteria*

USES
48%
LESS
PLASTIC

per ounce vs.
7.5oz pumps

ENRICHED WITH
MOISTURIZERS

Crisp Clean

Hand Soap

REFILL

50 FL OZ (1.56 QT) 1.47 L

PS0013310

PRINCIPAL DISPLAY PANEL - 591 ml Bottle Label

Softsoap®
brand

Antibacterial
Eliminates 99.9% of Bacteria*

HAND SOAP
REFILL

USE ONLY WITH
SOFTSOAP®
ANTIBACTERIAL

Crisp Clean

Hand Soap

20 FL OZ (591 ml)

9943737